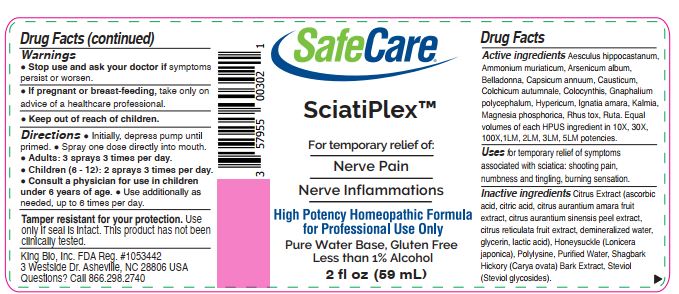 DRUG LABEL: Sciatiplex
NDC: 57955-3001 | Form: LIQUID
Manufacturer: King Bio Inc.
Category: homeopathic | Type: HUMAN OTC DRUG LABEL
Date: 20241120

ACTIVE INGREDIENTS: HORSE CHESTNUT 10 [hp_X]/59 mL; AMMONIUM CHLORIDE 10 [hp_X]/59 mL; ARSENIC TRIOXIDE 10 [hp_X]/59 mL; ATROPA BELLADONNA 10 [hp_X]/59 mL; CAPSICUM 10 [hp_X]/59 mL; CAUSTICUM 10 [hp_X]/59 mL; COLCHICUM AUTUMNALE BULB 10 [hp_X]/59 mL; CITRULLUS COLOCYNTHIS FRUIT PULP 10 [hp_X]/59 mL; PSEUDOGNAPHALIUM OBTUSIFOLIUM WHOLE 10 [hp_X]/59 mL; HYPERICUM PERFORATUM WHOLE 10 [hp_X]/59 mL; STRYCHNOS IGNATII SEED 10 [hp_X]/59 mL; KALMIA LATIFOLIA LEAF 10 [hp_X]/59 mL; MAGNESIUM PHOSPHATE, DIBASIC TRIHYDRATE 10 [hp_X]/59 mL; TOXICODENDRON PUBESCENS LEAF 10 [hp_X]/59 mL; RUTA GRAVEOLENS FLOWERING TOP 10 [hp_X]/59 mL
INACTIVE INGREDIENTS: ASCORBIC ACID; CITRIC ACID MONOHYDRATE; CITRUS AURANTIUM FRUIT OIL; ORANGE PEEL; CITRUS RETICULATA FRUIT OIL; WATER; GLYCERIN; LACTIC ACID, UNSPECIFIED FORM; LONICERA JAPONICA FLOWER; POLYEPSILON-LYSINE (4000 MW); CARYA OVATA BARK; STEVIOL

SciatiPlex

Warnings

Stop use and ask your doctor if symptoms
persist or worsen.

If pregnant or breast-feeding, take only on
advice of a healthcare professional.

Keep out of reach of children.

Reference image: SciatiPlex.jpg

Keep out of reach of children.

Reference image: SciatiPlex.jpg

Directions

Initially, depress pump until
primed.

Spray one dose directly into mouth.

Adults: 3 sprays 3 times per day.

Children (6 - 12): 2 sprays 3 times per day.

Consult a physician for use in children
under 6 years of age.

Use additionally as
needed, up to 6 times per day.

Reference image: SciatiPlex.jpg

OTHER SAFETY INFORMATION

Tamper resistant for your protection. Use
only if seal is intact. This product has not been
clinically tested.

King Bio, Inc. FDA Reg. #1053442
3 Westside Dr. Asheville, NC 28806 USA
Questions? Call 866.298.2740

Reference image: SciatiPlex.jpg

Active ingredients

Aesculus hippocastanum,
Ammonium muriaticum, Arsenicum album,
Belladonna, Capsicum annuum, Causticum,
Colchicum autumnale, Colocynthis, Gnaphalium
polycephalum, Hypericum, Ignatia amara, Kalmia,
Magnesia phosphorica, Rhus tox, Ruta.

Equal volumes of each HPUS ingredient in 10X, 30X, 100X, 1LM, 2LM, 3LM, 5LM potencies.

Reference image: SciatiPlex.jpg

Uses

For temporary relief of symptoms
associated with sciatica: shooting pain,
numbness and tingling, burning sensation.

Reference image: SciatiPlex.jpg

Inactive ingredients

Citrus Extract (ascorbic acid, citric acid, citrus aurantium amara fruit extract, citrus aurantium sinensis peel extract, citrus reticulata fruit extract, demineralized water, glycerin, lactic acid), Honeysuckle (Lonicera japonica), Polylysine, Purified Water, Shagbark Hickory (Carya ovata) Bark Extract, Steviol (Steviol glycosides).

Reference image: SciatiPlex.jpg

PURPOSE

Uses for temporary relief of: sciatica:

shooting pain

numbness and tingling

burning sensation

Refernce image: SciatiPlex.jpg